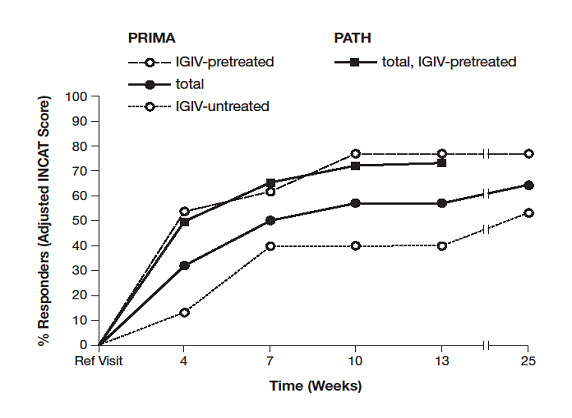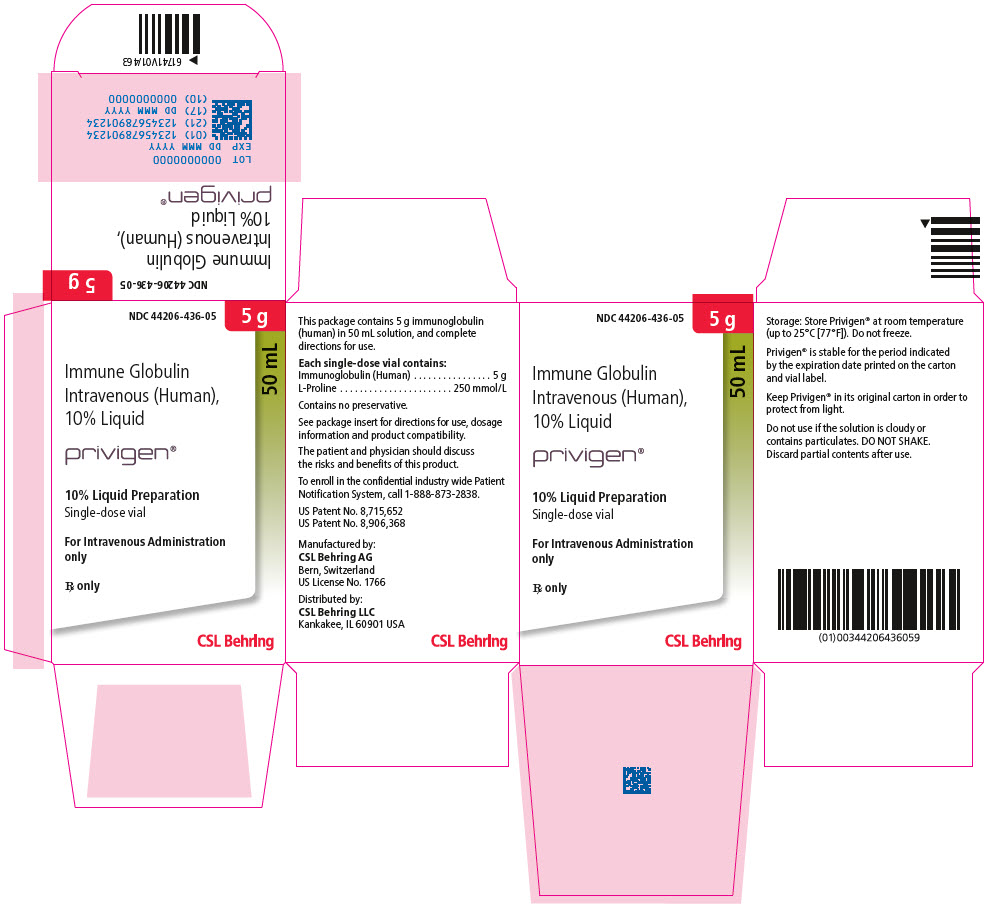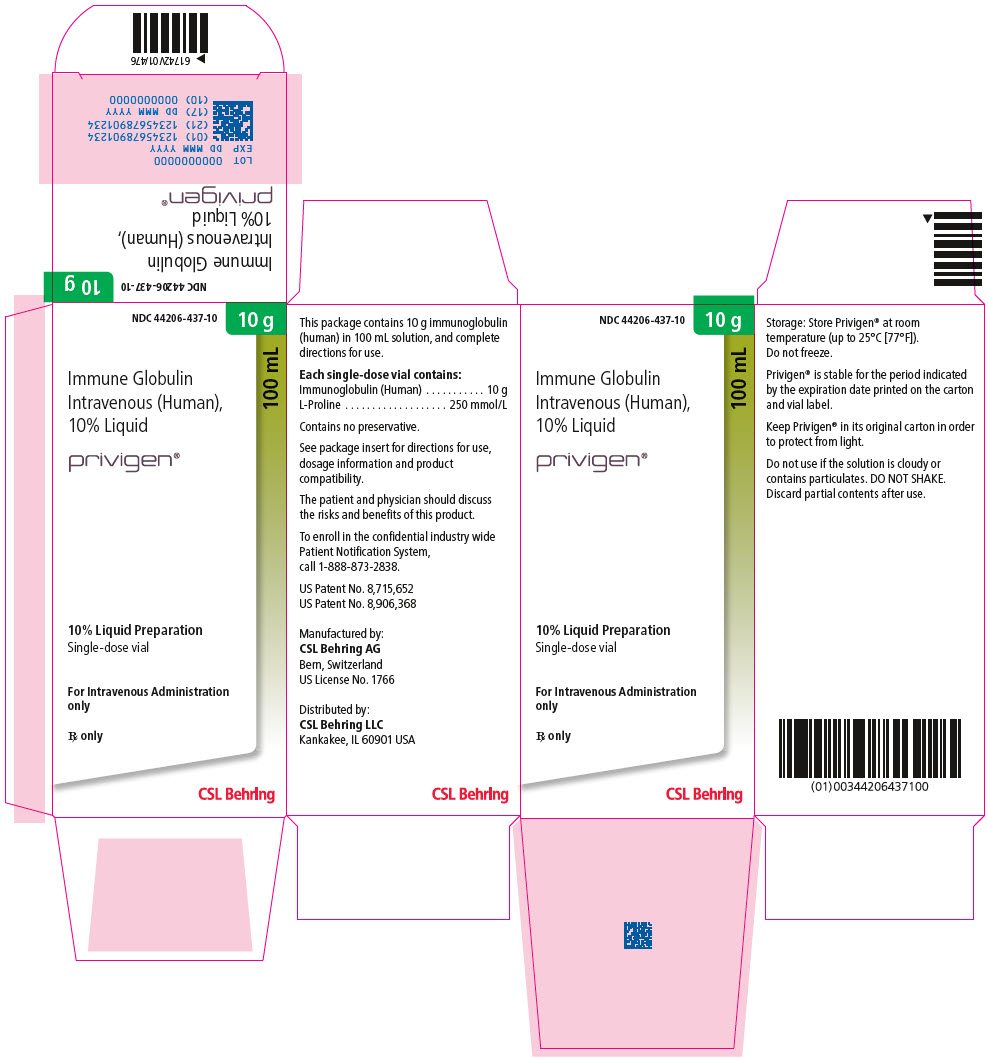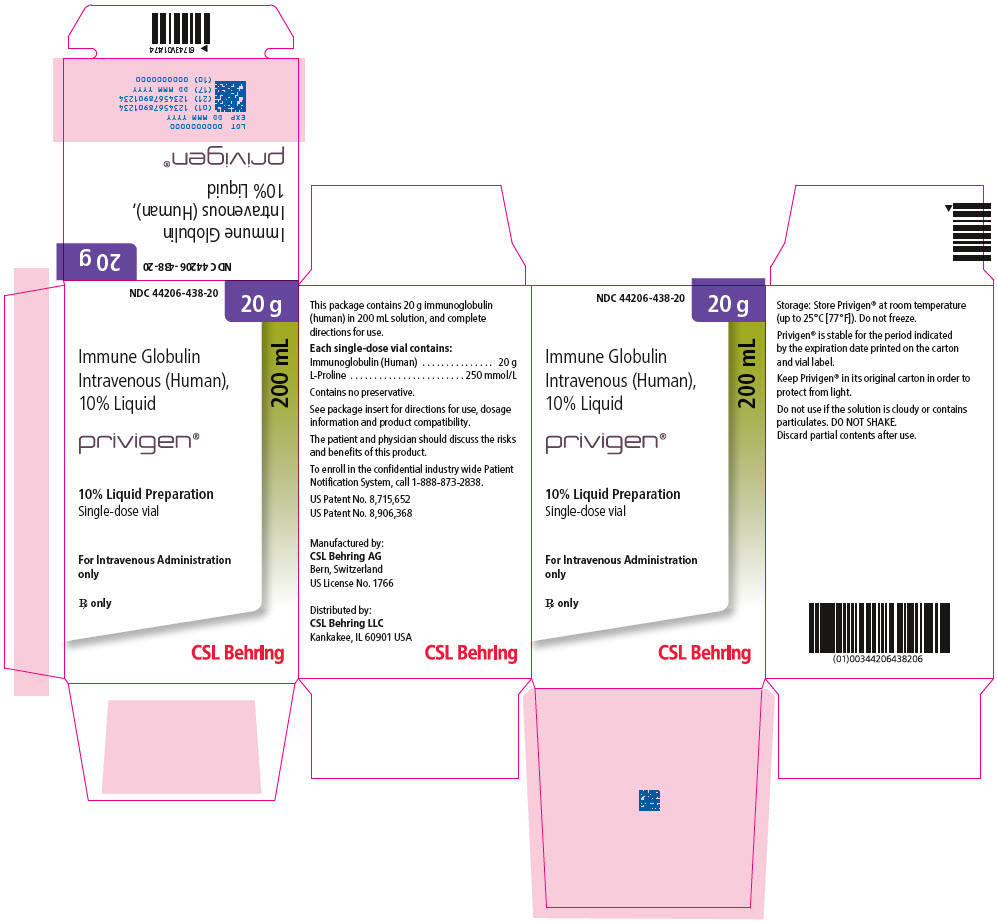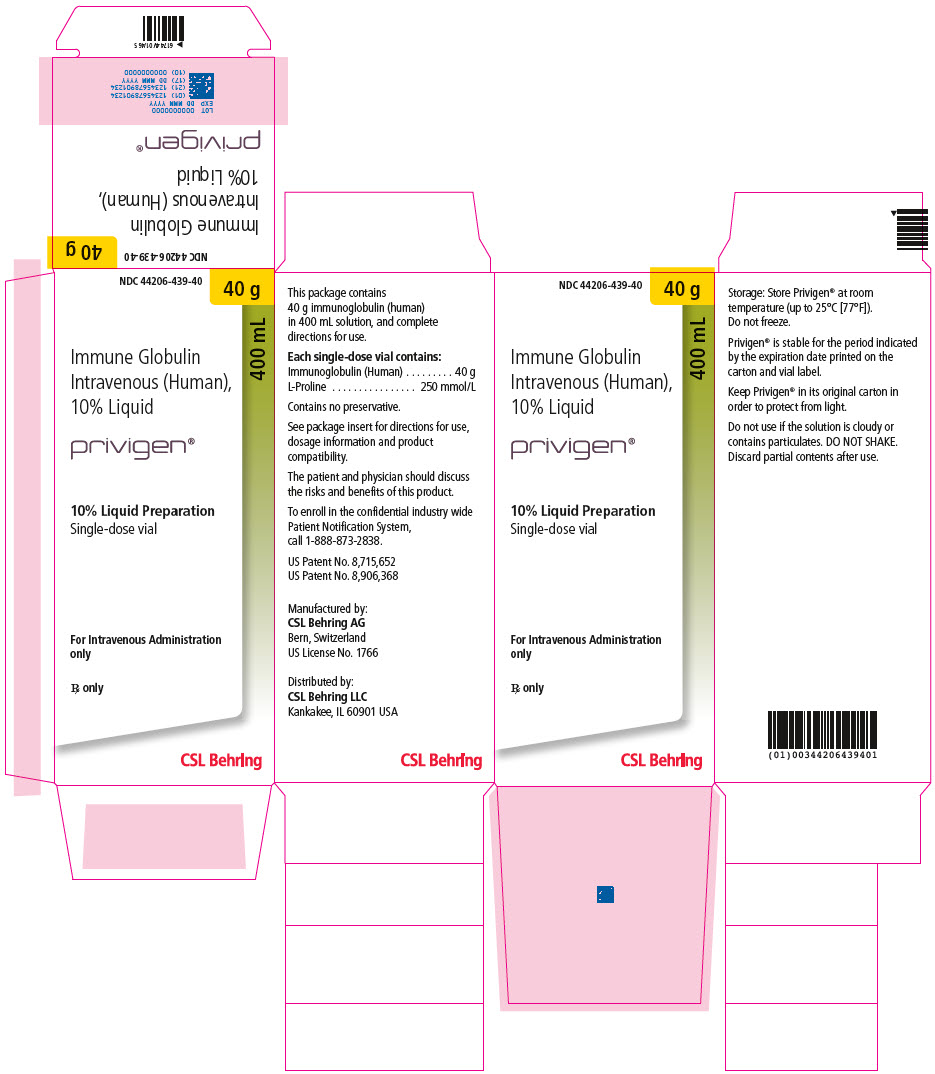 DRUG LABEL: Privigen
NDC: 44206-436 | Form: LIQUID
Manufacturer: CSL Behring AG
Category: other | Type: PLASMA DERIVATIVE
Date: 20250522

ACTIVE INGREDIENTS: Human Immunoglobulin G 5 g/50 mL
INACTIVE INGREDIENTS: Human Immunoglobulin A; Albumin Human; proline

HIGHLIGHTS OF PRESCRIBING INFORMATION

These highlights do not include all the information needed to use PRIVIGEN safely and effectively. See full prescribing information for PRIVIGEN.
PRIVIGEN, Immune Globulin Intravenous (Human), 10% Liquid, for intravenous use
Initial U.S. Approval: 2007

WARNING: THROMBOSIS, RENAL DYSFUNCTION AND ACUTE RENAL FAILURE

See full prescribing information for complete boxed warning.

- Thrombosis may occur with immune globulin products, including PRIVIGEN. Risk factors may include: advanced age, prolonged immobilization, hypercoagulable conditions, history of venous or arterial thrombosis, use of estrogens, indwelling vascular catheters, hyperviscosity, and cardiovascular risk factors. (5.3)
- Renal dysfunction, acute renal failure, osmotic nephrosis, and death may occur with immune globulin intravenous (IGIV) products in predisposed patients. Renal dysfunction and acute renal failure occur more commonly in patients receiving IGIV products containing sucrose. PRIVIGEN does not contain sucrose. (5.2)
- For patients at risk of thrombosis, renal dysfunction or failure, administer PRIVIGEN at the minimum dose and infusion rate practicable. Ensure adequate hydration in patients before administration. Monitor for signs and symptoms of thrombosis and assess blood viscosity in patients at risk for hyperviscosity. (5.2, 5.3)

1 INDICATIONS AND USAGE

PRIVIGEN is an Immune Globulin Intravenous (Human), 10% Liquid indicated for the treatment of:

- Primary humoral immunodeficiency (PI) (1.1)
- Chronic immune thrombocytopenic purpura (ITP) in patients aged 15 years and older (1.2)
- Chronic inflammatory demyelinating polyneuropathy (CIDP) in adults (1.3)

Limitations of Use:

Maintenance therapy in CIDP has not been studied beyond 6 months. (1.3)

2 DOSAGE AND ADMINISTRATION

For Intravenous Use Only

Indication | Dose | Initial Infusion Rate | Maintenance Infusion Rate (as tolerated)
PI | 200-800 mg/kg every 3-4 weeks | 0.5 mg/kg/min | Increase to 8 mg/kg/min
ITP | 1 g/kg for 2 consecutive days | 0.5 mg/kg/min | Increase to 4 mg/kg/min
CIDP | Loading dose: 2 g/kg in divided doses over 2 to 5 consecutive days Maintenance dose: 1 g/kg administered in 1 to 2 infusions on consecutive days, every 3 weeks | 0.5 mg/kg/min | Increase to 8 mg/kg/min

3 DOSAGE FORMS AND STRENGTHS

PRIVIGEN is a liquid solution containing 10% IgG (0.1 g/mL). (3)

4 CONTRAINDICATIONS

- History of anaphylactic or severe systemic reaction to human immune globulin (4)
- Hyperprolinemia (PRIVIGEN contains the stabilizer L-proline) (4)
- IgA-deficient patients with antibodies to IgA and a history of hypersensitivity (4)

5 WARNINGS AND PRECAUTIONS

- IgA-deficient patients with antibodies to IgA are at greater risk of developing severe hypersensitivity and anaphylactic reactions. (5.1)
- Monitor renal function in patients at risk of developing renal failure. (5.2)
- Hyperproteinemia, hyperviscosity, and hyponatremia may occur. (5.4)
- Aseptic meningitis syndrome (AMS) may occur, especially with high doses or rapid infusion. (5.5)
- Hemolysis that is either intravascular or due to enhanced red blood cell sequestration may occur. Risk factors include high doses and non-O blood group. Closely monitor patients for hemolysis and hemolytic anemia (5.6)
- Elevations of blood pressure (including cases of hypertensive urgency) have been observed during/shortly following PRIVIGEN infusion. (5.7)
- Monitor patients for pulmonary adverse reactions (transfusion-related acute lung injury [TRALI]). (5.8)
- PRIVIGEN is made from human blood and may contain infectious agents. (5.10)

6 ADVERSE REACTIONS

The most common adverse reactions (incidence >5%) were:

- PI –headache, fatigue, nausea, chills, vomiting, back pain, pain, elevated body temperature, abdominal pain, diarrhea, cough, stomach discomfort, chest pain, joint swelling/effusion, influenza-like illness, pharyngolaryngeal pain, urticaria, and dizziness. (6.1)
- Chronic ITP –laboratory findings consistent with hemolysis , headache, elevated body temperature, anemia, nausea, and vomiting. (6.1)
- CIDP –headache, asthenia, hypertension, nausea, pain in extremity, hemolysis, influenza like illness, leukopenia, and rash. (6.1)

To report SUSPECTED ADVERSE REACTIONS, contact CSL Behring Pharmacovigilance at 1-866-915-6958 or FDA at 1-800-FDA-1088 or www.fda.gov/medwatch.

7 DRUG INTERACTIONS

The passive transfer of antibodies may:

- Lead to misinterpretation of the results of serological testing. (5.11)
- Interfere with the response to live virus vaccines. (7.1)

8 USE IN SPECIFIC POPULATIONS

Geriatric: In patients over age 65 or in any patient at risk of developing renal insufficiency, do not exceed the recommended dose, and infuse PRIVIGEN at the minimum rate practicable. (8.5)

FULL PRESCRIBING INFORMATION

WARNING: THROMBOSIS, RENAL DYSFUNCTION AND ACUTE RENAL FAILURE

Thrombosis may occur with immune globulin products^1-3, including PRIVIGEN. Risk factors may include: advanced age, prolonged immobilization, hypercoagulable conditions, history of venous or arterial thrombosis, use of estrogens, indwelling central vascular catheters, hyperviscosity, and cardiovascular risk factors. Thrombosis may occur in the absence of known risk factors [see Warnings and Precautions (5.3), Patient Counseling Information (17)].

Renal dysfunction, acute renal failure, osmotic nephrosis, and death may occur with immune globulin intravenous (IGIV) products in predisposed patients. Patients predisposed to renal dysfunction include those with any degree of pre-existing renal insufficiency, diabetes mellitus, age greater than 65, volume depletion, sepsis, paraproteinemia, or patients receiving known nephrotoxic drugs.

Renal dysfunction and acute renal failure occur more commonly in patients receiving IGIV products containing sucrose.^4 PRIVIGEN does not contain sucrose.

For patients at risk of thrombosis, renal dysfunction or failure, administer PRIVIGEN at the minimum dose and infusion rate practicable. Ensure adequate hydration in patients before administration. Monitor for signs and symptoms of thrombosis and assess blood viscosity in patients at risk for hyperviscosity [see Dosage and Administration (2.5), Warnings and Precautions (5.2, 5.3)].

1 INDICATIONS AND USAGE

PRIVIGEN is an Immune Globulin Intravenous (Human), 10% Liquid indicated for the treatment of the following conditions.

1.1 Primary Humoral Immunodeficiency

PRIVIGEN is indicated as replacement therapy for primary humoral immunodeficiency (PI). This includes, but is not limited to, the humoral immune defect in congenital agammaglobulinemia, common variable immunodeficiency (CVID), X-linked agammaglobulinemia, Wiskott-Aldrich syndrome, and severe combined immunodeficiencies.

1.2 Chronic Immune Thrombocytopenic Purpura

PRIVIGEN is indicated for the treatment of patients age 15 years and older with chronic immune thrombocytopenic purpura (ITP) to raise platelet counts.

1.3 Chronic Inflammatory Demyelinating Polyneuropathy

PRIVIGEN is indicated for the treatment of adults with chronic inflammatory demyelinating polyneuropathy (CIDP) to improve neuromuscular disability and impairment.

Limitation of Use:

PRIVIGEN maintenance therapy in CIDP has not been studied for periods longer than 6 months. After responding during an initial treatment period, not all patients require indefinite maintenance therapy with PRIVIGEN in order to remain free of CIDP symptoms. Individualize the duration of any treatment beyond 6 months based upon the patient's response and demonstrated need for continued therapy.

2 DOSAGE AND ADMINISTRATION

Table 1. Recommended Dosage and Administration for PRIVIGEN
Indication | Dose | Initial infusion rate | Maintenance infusion rate (as tolerated)
Primary Immunodeficiency | 200-800 mg/kg (2-8 mL/kg) every 3-4 weeks | 0.5 mg/kg/min (0.005 mL/kg/min) | Increase to 8 mg/kg/min (0.08 mL/kg/min)
Chronic Immune Thrombocytopenic Purpura | 1 g/kg (10 mL/kg) for 2 consecutive days | 0.5 mg/kg/min (0.005 mL/kg/min) | Increase to 4 mg/kg/min (0.04 mL/kg/min)
Chronic Inflammatory Demyelinating Polyneuropathy | Loading dose: 2 g/kg (20 mL/kg) in divided doses over 2 to 5 consecutive days Maintenance dose: 1 g/kg (10 mL/kg) administered in 1 to 2 infusions on consecutive days, every 3 weeks | 0.5 mg/kg/min (0.005 mL/kg/min) | Increase to 8 mg/kg/min (0.08 mL/kg/min)

2.1 Dosage for Primary Humoral Immunodeficiency (PI)

As there are significant differences in the half-life of IgG among patients with PI, the frequency and amount of immunoglobulin therapy may vary from patient to patient. The proper amount can be determined by monitoring clinical response.

The recommended dose of PRIVIGEN for patients with PI is 200 to 800 mg/kg (2 to 8 mL/kg), administered every 3 to 4 weeks. If a patient misses a dose, administer the missed dose as soon as possible, and then resume scheduled treatments every 3 or 4 weeks, as applicable.

Adjust the dosage over time to achieve the desired serum IgG trough levels and clinical responses. No randomized, controlled trial data are available to determine an optimal trough level in patients receiving immune globulin therapy.

Measles Exposure

If a patient has been exposed to measles, it may be prudent to administer an extra dose of Immune Globulin Intravenous as soon as possible and within 6 days of exposure. A dose of 400 mg/kg should provide a serum level > 240 mIU/mL of measles antibodies for at least two weeks.

If a patient is at risk of future measles exposure and receives a dose of less than 530 mg/kg every 3-4 weeks, the dose should be increased to at least 530 mg/kg. This should provide a serum level of 240 mIU/mL of measles antibodies for at least 22 days after infusion.

2.2 Dosage for Chronic Immune Thrombocytopenic Purpura (ITP)

The recommended dose of PRIVIGEN for patients with chronic ITP is 1 g/kg (10 mL/kg) administered daily for 2 consecutive days, resulting in a total dosage of 2 g/kg.

Carefully consider the relative risks and benefits before prescribing the high dose regimen (e.g., 1 g/kg/day for 2 days) in patients at increased risk of thrombosis, hemolysis, acute kidney injury, or volume overload [see Warnings and Precautions (5.9)].

2.3 Dosage for Chronic Inflammatory Demyelinating Polyneuropathy (CIDP)

PRIVIGEN may be initially administered as a total loading dose of 2 g/kg (20 mL/kg) given in divided doses over two to five consecutive days. PRIVIGEN may be administered as a maintenance infusion of 1 g/kg (10 mL/kg) administered in a single infusion given in one day or divided into two doses given on two consecutive days, every 3 weeks. Maintenance therapy beyond 6 months has not been studied.

The recommended initial infusion rate is 0.5 mg/kg/min (0.005 mL/kg/min). If the infusion is well tolerated, the rate may be gradually increased to a maximum of 8 mg/kg/min (0.08 mL/kg/min). For patients judged to be at risk for thrombosis, renal dysfunction, or volume overload, administer PRIVIGEN at the minimum infusion rate practicable [see Warnings and Precautions (5.2, 5.3)].

2.4 Preparation and Handling

- PRIVIGEN is a clear or slightly opalescent, colorless to pale yellow solution. Inspect parenteral drug products visually for particulate matter and discoloration prior to administration, whenever solution and container permit. Do not use if the solution is cloudy, turbid, or if it contains particulate matter.
- DO NOT SHAKE.
- Do not freeze. Do not use if PRIVIGEN has been frozen.
- PRIVIGEN should be at room temperature (up to 25ºC [77ºF]) at the time of administration.
- Do not use PRIVIGEN beyond the expiration date on the product label.
- The PRIVIGEN vial is for single-use only. Promptly use any vial that has been entered. PRIVIGEN contains no preservative. Discard partially used vials or unused product in accordance with local requirements.
- Infuse PRIVIGEN using a separate infusion line. Prior to use, the infusion line may be flushed with Dextrose Injection, USP (D5W) or 0.9% Sodium Chloride for Injection, USP.
- Do not mix PRIVIGEN with other IGIV products or other intravenous medications. However, PRIVIGEN may be diluted with Dextrose Injection, USP (D5W).
- An infusion pump may be used to control the rate of administration.
- If large doses of PRIVIGEN are to be administered, several vials may be pooled using aseptic technique. Begin infusion within 8 hours of pooling.

2.5 Administration

PRIVIGEN is for intravenous administration only.

Monitor the patient's vital signs throughout the infusion. Slow or stop the infusion if adverse reactions occur. If symptoms subside promptly, the infusion may be resumed at a lower rate that is comfortable for the patient.

Ensure that patients with pre-existing renal insufficiency are not volume depleted. For patients judged to be at risk for renal dysfunction or thrombosis, administer PRIVIGEN at the minimum dose and infusion rate practicable, and discontinue PRIVIGEN administration if renal function deteriorates [see Boxed Warning, Warnings and Precautions (5.2, 5.3)].

The following patients may be at risk of developing systemic reactions (mimicking symptoms of an inflammatory response or infection) on rapid infusion of PRIVIGEN (greater than 4 mg/kg/min [0.04 mL/kg/min]): 1) those who have never received PRIVIGEN or another IgG product or who have not received it within the past 8 weeks, and 2) those who are switching from another IgG product. These patients should be started at a slow rate of infusion (e.g., 0.5 mg/kg/min [0.005 mL/kg/min] or less) and gradually increase as tolerated.

3 DOSAGE FORMS AND STRENGTHS

PRIVIGEN is a liquid solution containing 10% IgG (0.1 g/mL) for intravenous infusion.

4 CONTRAINDICATIONS

- PRIVIGEN is contraindicated in patients who have a history of anaphylactic or severe systemic reaction to the administration of human immune globulin.
- PRIVIGEN is contraindicated in patients with hyperprolinemia because it contains the stabilizer L-proline [see Description (11)].
- PRIVIGEN is contraindicated in IgA-deficient patients with antibodies to IgA and a history of hypersensitivity [see Warnings and Precautions (5.1)].

5 WARNINGS AND PRECAUTIONS

5.1 Hypersensitivity

Severe hypersensitivity reactions may occur [see Contraindications (4)]. In case of hypersensitivity, discontinue the PRIVIGEN infusion immediately and institute appropriate treatment. Medications such as epinephrine should be available for immediate treatment of acute hypersensitivity reactions.

PRIVIGEN contains trace amounts of IgA (≤25 mcg/mL) [see Description (11)]. Individuals with IgA deficiency can develop anti-IgA antibodies and anaphylactic reactions (including anaphylaxis and shock) after administration of blood components containing IgA. Patients with known antibodies to IgA may have a greater risk of developing potentially severe hypersensitivity and anaphylactic reactions with administration of PRIVIGEN. PRIVIGEN is contraindicated in patients with antibodies against IgA and a history of hypersensitivity.

5.2 Renal Dysfunction and Acute Renal Failure

Renal dysfunction, acute renal failure, osmotic nephrosis, and death may occur with immune globulin intravenous (IGIV) products in predisposed patients. Renal dysfunction and acute renal failure occur more commonly in patients receiving IGIV products containing sucrose. ^4 PRIVIGEN does not contain sucrose. Acute renal failure may also occur as a result of PRIVIGEN-induced hemolysis. Ensure that patients are not volume depleted and assess renal function, including measurement of blood urea nitrogen (BUN) and serum creatinine, before the initial infusion of PRIVIGEN and at appropriate intervals thereafter.

Periodic monitoring of renal function and urine output is particularly important in patients judged to be at increased risk of developing acute renal failure.^4 If renal function deteriorates, consider discontinuing PRIVIGEN. For patients judged to be at risk of developing renal dysfunction because of pre-existing renal insufficiency, or predisposition to acute renal failure (such as those with diabetes mellitus or hypovolemia, those who are obese, those who use concomitant nephrotoxic medicinal products, or those who are over 65 years of age), administer PRIVIGEN at the minimum rate of infusion practicable [see Boxed Warning, Dosage and Administration (2.5)].

5.3 Thrombosis

Thrombosis may occur following treatment with immune globulin products^1-3, including PRIVIGEN. Risk factors may include: advanced age, prolonged immobilization, hypercoagulable conditions, history of venous or arterial thrombosis, use of estrogens, indwelling central vascular catheters, hyperviscosity, and cardiovascular risk factors. Thrombosis may occur in the absence of known risk factors.

Consider baseline assessment of blood viscosity in patients at risk for hyperviscosity, including those with cryoglobulins, fasting chylomicronemia/markedly high triacylglycerols (triglycerides), or monoclonal gammopathies. For patients at risk of thrombosis, administer PRIVIGEN at the minimum dose and infusion rate practicable. Ensure adequate hydration in patients before administration. Monitor for signs and symptoms of thrombosis and assess blood viscosity in patients at risk for hyperviscosity [see Boxed Warning, Dosage and Administration (2.5), Patient Counseling Information (17)].

5.4 Hyperproteinemia, Increased Serum Viscosity, and Hyponatremia

Hyperproteinemia, increased serum viscosity, and hyponatremia may occur following treatment with IGIV products, including PRIVIGEN. The hyponatremia is likely to be a pseudohyponatremia, as demonstrated by a decreased calculated serum osmolality or elevated osmolar gap. It is critical to distinguish true hyponatremia from pseudohyponatremia, as treatment aimed at decreasing serum free water in patients with pseudohyponatremia may lead to volume depletion, a further increase in serum viscosity, and a possible predisposition to thromboembolic events.^5

5.5 Aseptic Meningitis Syndrome (AMS)

AMS may occur infrequently following treatment with PRIVIGEN [see Adverse Reactions (6)] and other human immune globulin products. Discontinuation of treatment has resulted in remission of AMS within several days without sequelae.^6 AMS usually begins within several hours to 2 days following IGIV treatment.

AMS is characterized by the following signs and symptoms: severe headache, nuchal rigidity, drowsiness, fever, photophobia, painful eye movements, nausea, and vomiting. Cerebrospinal fluid (CSF) studies are frequently positive with pleocytosis up to several thousand cells per cubic millimeter, predominantly from the granulocytic series, and with elevated protein levels up to several hundred mg/dL, but negative culture results. Conduct a thorough neurological examination on patients exhibiting such signs and symptoms, including CSF studies, to rule out other causes of meningitis.

AMS may occur more frequently in association with high doses (2 g/kg) and/or rapid infusion of IGIV [see Dosage and Administration (2.5)].

5.6 Hemolysis

PRIVIGEN may contain blood group antibodies that can act as hemolysins and induce in vivo coating of red blood cells (RBCs) with immunoglobulin, causing a positive direct antiglobulin test (DAT) (Coombs' test) result and hemolysis.^7-9 Delayed hemolytic anemia can develop subsequent to PRIVIGEN therapy due to enhanced RBC sequestration, and acute hemolysis, consistent with intravascular hemolysis, has been reported.^10 Cases of severe hemolysis-related renal dysfunction/failure or disseminated intravascular coagulation have occurred following infusion of PRIVIGEN.

The following risk factors may be associated with the development of hemolysis: high doses (e.g., ≥2 g/kg), given either as a single administration or divided over several days, and non-O blood group.^11 Other individual patient factors, such as an underlying inflammatory state (as may be reflected by, for example, elevated C-reactive protein or erythrocyte sedimentation rate), have been hypothesized to increase the risk of hemolysis following administration of IGIV,^12 but their role is uncertain. Hemolysis has been reported following administration of IGIV for a variety of indications, including ITP, CIDP, and PI.^9

Closely monitor patients for clinical signs and symptoms of hemolysis, particularly patients with risk factors noted above and those with pre-existing anemia and/or cardiovascular or pulmonary compromise. Consider appropriate laboratory testing in higher risk patients, including measurement of hemoglobin or hematocrit prior to infusion and within approximately 36 hours and again 7 to 10 days post infusion. If clinical signs and symptoms of hemolysis or a significant drop in hemoglobin or hematocrit have been observed, perform additional confirmatory laboratory testing. If transfusion is indicated for patients who develop hemolysis with clinically compromising anemia after receiving IGIV, perform adequate cross-matching to avoid exacerbating on-going hemolysis.

5.7 Hypertension

Elevations of systolic blood pressure to ≥180 mm Hg and/or of diastolic blood pressure to >120 mm Hg (hypertensive urgency) have been observed during and/or shortly following infusion of PRIVIGEN. These blood pressure elevations were resolved or significantly improved within hours with either observation alone or changes in oral anti-hypertensive therapy [see Adverse Reactions (6.1)]. Such elevations were reported more often among patients with a history of hypertension. Check patients for a history of hypertension and current antihypertensive medication use. Monitor blood pressure prior to, during, and following PRIVIGEN infusion.

5.8 Transfusion-Related Acute Lung Injury (TRALI)

Noncardiogenic pulmonary edema may occur following treatment with IGIV products, including PRIVIGEN.^13 TRALI is characterized by severe respiratory distress, pulmonary edema, hypoxemia, normal left ventricular function, and fever. Symptoms typically appear within 1 to 6 hours following treatment.

Monitor patients for pulmonary adverse reactions. If TRALI is suspected, perform appropriate tests for the presence of anti-neutrophil antibodies and anti-human leukocyte antigen (HLA) antibodies in both the product and the patient's serum.

TRALI may be managed using oxygen therapy with adequate ventilatory support.

5.9 Volume Overload

Carefully consider the relative risks and benefits before prescribing the high dose regimen (for chronic ITP and CIDP) in patients at increased risk of thrombosis, hemolysis, acute kidney injury, or volume overload.

5.10 Transmissible Infectious Agents

Because PRIVIGEN is made from human blood, it may carry a risk of transmitting infectious agents (eg, viruses, the variant Creutzfeldt Jakob disease [vCJD] agent and, theoretically, the Creutzfeldt Jakob disease [CJD] agent). The risk of infectious agent transmission has been reduced by screening plasma donors for prior exposure to certain viruses, testing for the presence of certain current virus infections, and including virus inactivation/removal steps in the manufacturing process for PRIVIGEN.

Report any infection thought to be possibly transmitted by PRIVIGEN to CSL Behring Pharmacovigilance at 1-866-915-6958.

5.11 Interference with Laboratory Tests

Various passively transferred antibodies in immunoglobulin preparations may lead to misinterpretation of the results of serological testing.

6 ADVERSE REACTIONS

The following important adverse reactions are reported with IGIV: hypersensitivity, renal dysfunction and acute renal failure, thrombosis, hyperproteinemia, increased serum viscosity, hyponatremia, aseptic meningitis syndrome, hemolysis, hypertension, transfusion related acute lung injury, volume overload, and transmissible infectious agents [see Warnings and Precautions (5)] and are described elsewhere in the prescribing information.

Adverse reactions (ARs) [see Adverse Reactions (6.1)] are defined as adverse events at least possibly related or events occurring during or within 72 hours of a PRIVIGEN infusion.

Primary Humoral Immunodeficiency

The most serious adverse reaction observed in clinical study subjects receiving PRIVIGEN for PI was hypersensitivity in one subject [see Warnings and Precautions (5.1)]. The most common adverse reactions observed in >5% of clinical study subjects with PI were headache, fatigue, nausea, chills, vomiting, back pain, pain, elevated body temperature, abdominal pain, diarrhea, cough, stomach discomfort, chest pain, joint swelling/effusion, influenza-like illness, pharyngolaryngeal pain, urticaria, and dizziness.

Chronic Immune Thrombocytopenic Purpura

The most serious adverse reactions observed in the premarketing clinical study subjects receiving PRIVIGEN for chronic ITP were aseptic meningitis syndrome in one subject and hemolysis in two subjects [see Warnings and Precautions (5.5, 5.6)]. A total of 8 subjects (14%) in the premarketing ITP study experienced hemolysis as documented from clinical laboratory data. No serious adverse reactions were observed in the postmarketing chronic ITP study. A total of 12 subjects (21%) in the postmarketing ITP study were adjudicated to have mild hemolysis as documented from clinical laboratory data [see Warnings and Precautions (5.6)]. The most common adverse reactions observed in >5% of subjects in both clinical studies of subjects with chronic ITP were laboratory findings consistent with hemolysis (hemoglobin and hematocrit decrease without blood loss in conjunction with positive direct antiglobulin test (DAT) and elevated blood lactate dehydrogenase (LDH) and/or indirect bilirubin), headache, elevated body temperature, anemia, nausea, and vomiting.

Chronic Inflammatory Demyelinating Polyneuropathy

The most serious adverse reactions observed in clinical study subjects receiving PRIVIGEN for CIDP was hemolysis. The most common adverse reactions observed in >5% of subjects in both clinical studies of subjects with CIDP were headache, asthenia, hypertension, nausea, pain in extremity, hemolysis, influenza like illness, leukopenia, and rash.

6.1 Clinical Trials Experience

Because different clinical trials are conducted under widely varying conditions, adverse reaction rates observed in the clinical trials of a drug cannot be directly compared to rates in the clinical trials of another drug and may not reflect the rates observed in clinical practice.

Treatment of Primary Humoral Immunodeficiency

In a prospective, open-label, single-arm, multicenter clinical study, 80 subjects with PI (with a diagnosis of XLA or CVID) received PRIVIGEN every 3 or 4 weeks for up to 12 months [see Clinical Studies (14.1)]. All subjects had been on regular IGIV replacement therapy for at least 6 months prior to participating in the study. Subjects ranged in age from 3 to 69; 46 (57.5%) were male and 34 (42.5%) were female.

The safety analysis included all 80 subjects, 16 (20%) on the 3-week schedule and 64 (80%) on the 4-week schedule. The median dose of PRIVIGEN administered was 428 mg/kg (3-week schedule) or 441 mg/kg (4-week schedule) and ranged from 200 to 888 mg/kg. A total of 1038 infusions of PRIVIGEN were administered, 272 in the 3-week schedule and 766 in the 4-week schedule.

Routine premedication was not allowed. However, subjects who experienced two consecutive infusion-related ARs that were likely to be prevented by premedication were permitted to receive antipyretics, antihistamines, NSAIDs, or antiemetic agents. During the study, 8 (10%) subjects received premedication prior to 51 (4.9%) of the 1038 infusions administered.

Table 2 summarizes the most frequent ARs that occurred in >5% of subjects.

Table 2. PI Pivotal Study – ARs [ARs are defined as adverse events at least possibly related or events occurring during or within 72 hours of a PRIVIGEN infusion. Infections are excluded from this table.] Occurring in >5% of Subjects
AR | Number (%) of Subjects [n=80] | Number (Rate) of Infusions with AR [n=1038]
Headache | 36 (45.0) | 100 (0.096)
Fatigue | 13 (16.3) | 29 (0.028)
Nausea | 11 (13.8) | 23 (0.022)
Chills | 9 (11.3) | 15 (0.014)
Vomiting | 9 (11.3) | 15 (0.014)
Back pain | 8 (10.0) | 15 (0.014)
Pain | 7 (8.8) | 14 (0.013)
Elevated body temperature | 7 (8.8) | 12 (0.012)
Diarrhea | 6 (7.5) | 6 (0.006)
Cough | 5 (6.3) | 5 (0.005)
Stomach discomfort | 5 (6.3) | 5 (0.005)

Of the 192 ARs reported (including 5 serious, severe ARs described below) 91 were mild (awareness of sign, symptom or event, but easily tolerated), 81 were moderate (discomfort enough to cause interference with usual activity and may have warranted intervention), 19 were severe (incapacitating with inability to do usual activities or significantly affected clinical status, and warranted intervention), and 1 was of unknown severity.

The five serious ARs (hypersensitivity, chills, fatigue, dizziness, and increased body temperature, all severe), occurred in one subject, and resulted in the subject's withdrawal from the study. Two other subjects withdrew from the study due to ARs (chills and headache in one subject; vomiting in the other).

Seventy-seven of the 80 subjects enrolled in this study had a negative DAT at baseline. Of these 77 subjects, 36 (46.8%) developed a positive DAT at some time during the study. However, no subjects showed evidence of hemolytic anemia.

During this study, no subjects tested positive for infection due to human immunodeficiency virus (HIV), hepatitis B virus (HBV), hepatitis C virus (HCV), or B19 virus (B19V).

An extension of the study described above was conducted in 55 adult and pediatric subjects with PI to collect additional efficacy, safety, and tolerability data. This study included 45 subjects from the pivotal study who were receiving PRIVIGEN and 10 new subjects who were receiving another IGIV product prior to enrolling in the extension study. Subjects ranged in age from 4 to 81 years; 26 (47.3%) were male and 29 (52.7%) were female.

Subjects were treated with PRIVIGEN at median doses ranging from 286 to 832 mg/kg per infusion over a treatment period ranging from 1 to 27 months. Twelve (21.8%) subjects were on a 3-week treatment schedule with the number of infusions per subject ranging from 4 to 38 (median: 8 infusions); 43 (78%) subjects were on a 4-week schedule with the number of infusions ranging from 1 to 31 (median: 15 infusions). A total of 771 infusions were administered in this study.

In this study, subjects who continued from the pivotal study were permitted to receive infusions of PRIVIGEN at a rate up to 12 mg/kg/min (as opposed to the maximum of 8 mg/kg/min allowed in the pivotal study) at the discretion of the investigator based on individual tolerability. Twenty-three (51%) of the 45 subjects from the pivotal study (42% of the 55 subjects in the extension study) received 265 (38%) infusions at a maximum rate greater than the recommended rate of 8 mg/kg/min [see Dosage and Administration (2.5)]. The median of the maximum infusion rate in this subset was 12 mg/kg/min. However, because the study was not designed to compare infusion rates, no definitive conclusions regarding tolerability could be drawn for infusion rates higher than the recommended rate of 8 mg/kg/min.

Table 3 summarizes the ARs that occurred in >5% of subjects.

Table 3. PI Extension Study – ARs [Excluding infections.] Occurring in >5% of Subjects
AR | Number (%) of Subjects [n=55] | Number (Rate) of Infusions with AR [n=771]
Headache | 18 (32.7) | 76 (0.099)
Nausea | 6 (10.9) | 10 (0.013)
Elevated body temperature | 4 (7.3) | 12 (0.016)
Abdominal pain [Includes abdominal pain, abdominal pain upper, and abdominal pain lower.] | 4 (7.3) | 7 (0.009)
Chest pain | 3 (5.5) | 4 (0.005)
Chills | 3 (5.5) | 7 (0.009)
Joint swelling/effusion | 3 (5.5) | 7 (0.009)
Pain | 3 (5.5) | 6 (0.008)
Fatigue | 3 (5.5) | 5 (0.006)
Influenza-like illness | 3 (5.5) | 5 (0.006)
Pharyngolaryngeal pain | 3 (5.5) | 4 (0.005)
Urticaria | 3 (5.5) | 4 (0.005)
Dizziness | 3 (5.5) | 3 (0.004)
Note: The AR rates in this study cannot be compared directly to the rates in other IGIV studies, including the original pivotal study described earlier in this section, because (1) the extension study used an enriched population and (2) the selective use of higher infusion rates at the investigators' discretion in a subset of subjects may have introduced bias.

Of the 125 reported ARs, 76 were mild (did not interfere with routine activities), 40 were moderate (interfered somewhat with routine activities), and 9 were severe (impossible to perform routine activities).

Three subjects experienced ARs: dyspnea and pancytopenia in one subject, a transient ischemic attack 16 days after the infusion in one subject, and mild urticaria in one subject, resulting in the subject's withdrawal from the study.

Treatment of Chronic Immune Thrombocytopenic Purpura

In a prospective, open-label, single-arm, multicenter premarketing clinical study, 57 subjects with chronic ITP and a platelet count of 20 × 10^9/L or less received a total of 2 g/kg dose of PRIVIGEN administered as 1 g/kg infusions daily for 2 consecutive days [see Clinical Studies (14.2)]. Subjects ranged in age from 15 to 69; 23 (40%) were male and 34 (60%) were female.

Concomitant medications affecting platelets or other treatments for chronic ITP were not allowed. Thirty-two (56%) subjects received premedication with acetaminophen and/or an antihistamine.

Table 4 summarizes the most frequent ARs that occurred in >5% of subjects with chronic ITP.

Table 4. Chronic ITP Premarketing Clinical Study – ARs [ARs were defined as adverse events at least possibly related or events occurring during or within 72 hours after the end of a treatment cycle [two consecutive infusions].] Occurring in >5% of Subjects
AR | Number (%) of Subjects [n=57] | Number (Rate) of Infusions with AR [n=114]
Headache | 37 (64.9) | 52 (0.456)
Elevated body temperature | 21 (36.8) | 23 (0.202)
Positive DAT | 7 (12.3) | 8 (0.070)
Anemia | 6 (10.5) | 6 (0.053)
Nausea | 6 (10.5) | 8 (0.070)
Epistaxis | 6 (10.5) | 8 (0.070)
Vomiting | 6 (10.5) | 7 (0.061)
Blood bilirubin unconjugated increased | 6 (10.5) | 6 (0.053)
Blood bilirubin conjugated increased | 5 (8.8) | 5 (0.044)
Blood total bilirubin increased | 3 (5.3) | 3 (0.026)
Hematocrit decreased | 3 (5.3) | 3 (0.026)
Blood lactate dehydrogenase increased | 3 (5.3) | 3 (0.026)

Of the 149 non-serious ARs, 103 were mild (awareness of sign, symptom or event, but easily tolerated), 37 were moderate (discomfort enough to cause interference with usual activity and may have warranted intervention), and 9 were severe (incapacitating with inability to do usual activities or significantly affected clinical status, and warranted intervention).

One subject experienced a serious AR (aseptic meningitis).

Eight subjects, all of whom had a positive DAT, experienced transient drug-related hemolytic reactions, which were associated with elevated bilirubin, elevated lactate dehydrogenase, and a decrease in hemoglobin level within two days after the infusion of PRIVIGEN. Two of the eight subjects were clinically anemic but did not require clinical intervention; these cases resolved uneventfully.

Four other subjects with active bleeding were reported to have developed anemia without evidence of hemolysis.

In this study, there was a decrease in hemoglobin after the first PRIVIGEN infusion (median decrease of 1.2 g/dL by Day 8) followed by a return to near baseline by Day 29.

Fifty-six of the 57 subjects in this study had a negative DAT at baseline. Of these 56 subjects, 12 (21%) developed a positive DAT during the 29-day study period.

Postmarketing Commitment Study in Chronic Immune Thrombocytopenic Purpura

In a prospective, open-label, single-arm, multicenter postmarketing clinical study whose primary objective was to evaluate mechanisms of hemolysis, 57 subjects with chronic ITP and a platelet count of <30 × 10^9/L at screening were studied following treatment with PRIVIGEN. Twenty-one (21) subjects (37%) received 1 infusion of 1 g/kg on Day 1 and 36 subjects (63%) received 2 infusions each of 1 g/kg (Day 1 and Day 3). Concomitant medications affecting platelets or other treatments for chronic ITP were not allowed. Subjects received premedication with acetaminophen and/or an antihistamine [see Clinical Studies (14.3)].

The most frequent ARs (adverse events at least possibly related or events occurring during or within 72 hours after the end of treatment) that occurred in >5% of subjects with chronic ITP were headache (16 subjects [28%]) and pyrexia (3 subjects [5%]).

No subject experienced a serious adverse reaction.

Of the 23 non-serious ARs, 22 were mild (does not interfere with routine activities), 1 was moderate (interferes somewhat with routine activities), and none were severe (impossible to perform routine activities).

All 57 subjects had a negative DAT at baseline. Twenty-two (38%) developed a positive DAT by Day 4, 19 of these subjects were from blood group A.

Fifteen subjects were adjudicated by an independent expert committee, for presumptive/possible hemolysis, all of whom received 2 g/kg IGIV during the study [see Clinical Studies (14.3)]. Twelve subjects (21%) were judged to have mild hemolysis. In these 12 subjects there was a median hemoglobin drop from baseline at Day 9 (nadir) of -3.0 g/dL (range -0.9 to -5.8 g/dL) with Day 9 hemoglobin values ranging from 9.9 to 13.2 g/dL and a median drop from baseline in hemogloblin of -1.2 g/dL (range -0.1 to -2.7 g/dL) at Day 29 (end of study) with hemoglobin values ranging from 11.8 to 15.8 g/dL. Ten subjects were blood group A and 2 subjects were blood group B. These hemoglobin drops were transient and were followed by recovery or partial recovery by Day 29. One subject experienced mild dyspnea between Day 9 and Day 16; 1 subject experienced mild dizziness on Day 4. No subject was judged as having experienced clinically significant intravascular hemolysis. Three of the 15 adjudicated subjects were judged not to have experienced hemolysis.

Treatment of Chronic Inflammatory Demyelinating Polyneuropathy (CIDP)

In a prospective, open-label, single-arm, multicenter clinical study (PRIVIGEN Impact on Mobility and Autonomy [PRIMA]), 28 subjects with CIDP received a PRIVIGEN loading dose of 2 g/kg followed by PRIVIGEN maintenance doses of 1 g/kg every 3 weeks for up to 21 weeks with 3 week follow up [see Clinical Studies (14.4)]. Administration of the loading dose occurred over 2 days and the maintenance dose over 1 day in the majority of cases.

Table 5 summarizes the most frequent ARs that occurred in ≥5% of subjects with CIDP.

Table 5. CIDP Clinical Study – ARs [ARs were defined as adverse events at least possibly related or events occurring during or within 72 hours after IV infusion.] Occurring in ≥5% of Subjects
AR | Number (%) of Subjects [n=28] | Number (Rate) of Infusions with AR [n=259]
Headache | 8 (28.6) | 19 (0.073)
Asthenia | 4 (14.3) | 4 (0.015)
Hypertension | 4 (14.3) | 6 (0.023)
Nausea | 3 (10.7) | 3 (0.012)
Pain in extremity | 3 (10.7) | 3 (0.012)
Hemolysis | 2 (7.1) | 2 (0.008)
Influenza like illness | 2 (7.1) | 2 (0.008)
Leukopenia | 2 (7.1) | 2 (0.008)
Rash | 2 (7.1) | 2 (0.008)

Two hemolysis serious adverse reactions occurred after the start of the PRIVIGEN induction dose in subjects with non-O blood groups (A and AB). The reactions resolved after discontinuation without the need for transfusion.

Four subjects, three of whom had a history of hypertension, had reversible increases in systolic blood pressure to ≥180 mm Hg during or within 1 to 4 hours following PRIVIGEN infusion. One of these subjects who had a history of untreated hypertension had a reversible increase in diastolic blood pressure from 84 mm Hg pre-infusion to 135 mm Hg at 1 hour after the end of the infusion. All were resolved or significantly improved within 1 to 6 hours with either observation alone or changes in oral anti-hypertensive therapy.

A total of 71 ARs were reported: 46 were mild (does not interfere with routine activities), 23 were moderate (interferes somewhat with routine activities), and 2 were severe (impossible to perform routine activities) in intensity.

In a second prospective, open-label PRIVIGEN pre-randomization phase of a multicenter, randomized, double-blind, placebo-controlled clinical study (Polyneuropathy and Treatment with Hizentra [PATH]), 207 IGIV-pretreated subjects with CIDP received a PRIVIGEN loading dose of 2 g/kg followed by up to 4 PRIVIGEN maintenance doses of 1 g/kg every three weeks for up to 13 weeks. Additionally, 60 of these subjects received PRIVIGEN rescue treatment by the same dosing regimen following CIDP relapse during the double-blind post-randomization phase [see Clinical Studies (14.4)].

Eight subjects experienced a serious adverse reaction (acute rash cutaneous, blood pressure diastolic increased, exacerbation of CIDP [2], hypersensitivity, pulmonary embolism, respiratory failure, and migraine. The serious adverse reactions of pulmonary embolism and respiratory failure occurred in subjects with preexisting risk factors. All serious adverse reactions resolved without sequelae.

Adverse reactions that occurred in >5% of subjects with CIDP were headache (33 subjects, 15.9% [rate per infusion 56/1894, 0.030]).

A total of 225 ARs were reported: 160 were mild (is transient, does not usually interfere with routine activities but minimal treatment or therapeutic intervention may be required), 59 were moderate (interferes somewhat with routine activities and usually alleviated with specific intervention but poses no significant or permanent risk of harm), and 6 were severe (interrupts usual activities of daily living, significantly affects clinical status, or may require intensive therapeutic intervention) in intensity.

6.2 Postmarketing Experience

Because adverse reactions are reported voluntarily post-approval from a population of uncertain size, it is not always possible to reliably estimate the frequency of these reactions or establish a causal relationship to product exposure.

PRIVIGEN

The following adverse reactions have been identified during postmarketing use of PRIVIGEN. This list does not include reactions already reported in clinical studies with PRIVIGEN [see Adverse Reactions (6.1)].

- Blood and lymphatic system disorders: Decreased neutrophil count
- Infusion reactions: Changes in blood pressure, dyspnea, tachycardia, flushing
- Renal: hemoglobinuria/hematuria/chromaturia, renal failure
- Neurological: photophobia, cerebral edema
- Integumentary: pruritus

General

In addition, the following adverse reactions have been identified and reported with the use of immune globulin products.^14

- Infusion Reactions: Malaise, rigors
- Renal: Acute renal dysfunction/failure, osmotic nephropathy
- Respiratory: Apnea, Acute Respiratory Distress Syndrome (ARDS), TRALI, cyanosis, hypoxemia, pulmonary edema, bronchospasm
- Cardiovascular: Cardiac arrest, thromboembolism, vascular collapse, hypotension
- Neurological: Coma, loss of consciousness, seizures, tremor
- Integumentary: Stevens-Johnson syndrome, epidermolysis, erythema multiforme, bullous dermatitis
- Hematologic: Pancytopenia, leukopenia
- Gastrointestinal: Hepatic dysfunction

7 DRUG INTERACTIONS

7.1 Live Virus Vaccines

The passive transfer of antibodies with immunoglobulin administration may interfere with the response to live virus vaccines such as measles, mumps, rubella, and varicella [see Patient Counseling Information (17)].^15

Inform the immunizing physician of recent therapy with PRIVIGEN so that appropriate measures can be taken.

8 USE IN SPECIFIC POPULATIONS

8.1 Pregnancy

Risk Summary

No human data are available to indicate the presence or absence of drug-associated risk. Animal reproduction studies have not been conducted with PRIVIGEN. It is not known whether PRIVIGEN can cause fetal harm when administered to a pregnant woman or can affect reproduction capacity. Immune globulins cross the placenta from maternal circulation increasingly after 30 weeks of gestation.^16,17 PRIVIGEN should be given to pregnant women only if clearly needed. In the U.S. general population, the estimated background risk of major birth defects and miscarriage in clinically recognized pregnancies is 2-4% and 15-20%, respectively.

8.2 Lactation

Risk Summary

No human data are available to indicate the presence or absence of drug-associated risk. The developmental and health benefits of breastfeeding should be considered along with the mother's clinical need for PRIVIGEN and any potential adverse effects on the breastfed infant from PRIVIGEN or from the underlying maternal condition.

8.4 Pediatric Use

Treatment of Primary Humoral Immunodeficiency

PRIVIGEN was evaluated in 31 pediatric subjects (19 children and 12 adolescents) with PI (prospective, open label, single arm, multicenter clinical study). There were no apparent differences in the safety and efficacy profiles as compared to those in adult subjects. No pediatric-specific dose requirements were necessary to achieve the desired serum IgG levels. The safety and effectiveness of PRIVIGEN have not been studied in clinical trials in pediatric patients with PI who are under the age of 3.

Treatment of Chronic Immune Thrombocytopenic Purpura

The safety and effectiveness of PRIVIGEN have not been established in pediatric patients with chronic ITP who are under the age of 15.

Treatment of Chronic Inflammatory Demyelinating Polyneuropathy

The safety and effectiveness of PRIVIGEN have not been established in pediatric patients with CIDP who are under the age of 18.

8.5 Geriatric Use

Clinical studies of PRIVIGEN in PID and ITP did not include sufficient numbers of subjects age 65 and over to determine whether they respond differently from younger subjects.

The safety and effectiveness of PRIVIGEN in CIDP subjects age 65 and over was similar to those under age 65.

Use caution when administering PRIVIGEN to patients age 65 and over who are judged to be at increased risk of developing acute renal insufficiency and thrombosis [see Boxed Warning, Warnings and Precautions (5.2, 5.3)]. Do not exceed recommended doses, and administer PRIVIGEN at the minimum dose and infusion rate practicable.

10 OVERDOSAGE

Overdose may lead to fluid overload and hyperviscosity, particularly in the elderly and in patients with impaired renal function.

11 DESCRIPTION

PRIVIGEN is a ready-to-use, sterile, 10% protein liquid preparation of polyvalent human immunoglobulin G (IgG) for intravenous administration. PRIVIGEN has a purity of at least 98% IgG, consisting primarily of monomers. The balance consists of IgG dimers (≤12%), small amounts of fragments and polymers, and albumin. PRIVIGEN contains ≤25 mcg/mL IgA. The IgG subclass distribution is similar to that of normal human plasma. PRIVIGEN has an osmolality of approximately 320 mOsmol/kg (range: 240 to 440) and a pH of 4.8 (range: 4.6 to 5.0).

PRIVIGEN contains approximately 250 mmol/L (range: 210 to 290) of L-proline (a nonessential amino acid) as a stabilizer and trace amounts of sodium. PRIVIGEN contains no carbohydrate stabilizers (e.g., sucrose, maltose) and no preservative.

PRIVIGEN is prepared from large pools of human plasma by a combination of cold ethanol fractionation, octanoic acid fractionation, and anion exchange chromatography. The IgG proteins are not subjected to heating or to chemical or enzymatic modification. The Fc and Fab functions of the IgG molecule are retained. Fab functions tested include antigen binding capacities, and Fc functions tested include complement activation and Fc-receptor-mediated leukocyte activation (determined with complexed IgG). PRIVIGEN does not activate the complement system or prekallikrein in an unspecific manner.

To specifically reduce blood group A and B antibodies (isoagglutinins A and B) the manufacturing process for PRIVIGEN includes an immunoaffinity chromatography step.

All plasma units used in the manufacture of PRIVIGEN have been tested and approved for manufacture using FDA-licensed serological assays for hepatitis B surface antigen and antibodies to HCV and HIV-1/2 as well as FDA-licensed Nucleic Acid Testing (NAT) for HBV, HCV and HIV-1 and found to be nonreactive (negative). In addition, the plasma has been tested for B19 virus (B19V) DNA by NAT. Only plasma that passed virus screening is used for production, and the limit for B19V in the fractionation pool is set not to exceed 10^4 IU of B19V DNA per mL.

The manufacturing process for PRIVIGEN includes three steps to reduce the risk of virus transmission. Two of these are dedicated virus clearance steps: pH 4 incubation to inactivate enveloped viruses and virus filtration to remove, by size exclusion, both enveloped and non-enveloped viruses as small as approximately 20 nanometers. In addition, a depth filtration step contributes to the virus reduction capacity.

These steps have been independently validated in a series of in vitro experiments for their capacity to inactivate and/or remove both enveloped and non-enveloped viruses.

Table 6 shows the virus clearance during the manufacturing process for PRIVIGEN, expressed as the mean log10 reduction factor (LRF).

Table 6. Virus Inactivation/Removal in PRIVIGEN [The virus clearance of human parvovirus B19 was investigated experimentally at the pH 4 incubation step. The estimated LRF obtained was ≥5.6.]
 | HIV-1 | PRV | BVDV | WNV | EMCV | MVM
Virus property
Genome | RNA | DNA | RNA | RNA | RNA | DNA
Envelope | Yes | Yes | Yes | Yes | No | No
Size (nm) | 80-100 | 120-200 | 50-70 | 50-70 | 25-30 | 18-24
Manufacturing step | Mean LRF
pH 4 incubation | ≥5.6 | ≥6.1 | 4.6 | ≥7.8 | nt | nt
Depth filtration | ≥6.7 | ≥5.7 | 3.5±0.2 | 3.0±0.4 | 5.7±0.2 | 3.7±0.3
Virus filtration | ≥4.7 | ≥5.8 | ≥4.6 | ≥6.8 | ≥6.3 | ≥6.5
Overall reduction (log10 units) | ≥17.0 | ≥17.6 | ≥12.7 | ≥17.6 | ≥12.0 | ≥10.2
HIV-1, human immunodeficiency virus type 1, a model for HIV-1 and HIV-2; PRV, pseudorabies virus, a nonspecific model for large enveloped DNA viruses (eg, herpes virus); BVDV, bovine viral diarrhea virus, a model for hepatitis C virus; WNV, West Nile virus; EMCV, encephalomyocarditis virus, a model for hepatitis A virus; MVM, minute virus of mice, a model for a small highly resistant non-enveloped DNA virus (eg, parvovirus); LRF, log10 reduction factor; nt, not tested.

12 CLINICAL PHARMACOLOGY

12.1 Mechanism of Action

PRIVIGEN supplies a broad spectrum of opsonizing and neutralizing IgG antibodies against a wide variety of bacterial and viral agents. The mechanism of action has not been fully elucidated, but may include immunomodulatory effects.

12.3 Pharmacokinetics

Treatment of Primary Humoral Immunodeficiency

In the clinical study assessing the efficacy and safety of PRIVIGEN in 80 subjects with PI [see Clinical Studies (14.1)], serum concentrations of total IgG and IgG subclasses were measured in 25 subjects (ages 13 to 69) following the 7th infusion for the 3 subjects on the 3-week dosing interval and following the 5th infusion for the 22 subjects on the 4-week dosing interval. The dose of PRIVIGEN used in these subjects ranged from 200 mg/kg to 714 mg/kg. After the infusion, blood samples were taken until Day 21 and Day 28 for the 3-week and 4-week dosing intervals, respectively.

Table 7 summarizes the pharmacokinetic parameters of PRIVIGEN, based on serum concentrations of total IgG.

Table 7. PI Study – Pharmacokinetic Parameters of PRIVIGEN in Subjects
Parameter | 3-Week Dosing Interval (n=3) |  | 4-Week Dosing Interval (n=22)
Parameter | Mean (SD) | Median (Range) | Mean (SD) | Median (Range)
Cmax (peak, mg/dL) | 2,550 (400) | 2,340 (2,290-3,010) | 2,260 (530) | 2,340 (1,040-3,460)
Cmin (trough, mg/dL) | 1,230 (230) | 1,200 (1,020-1,470) | 1,000 (200) | 1,000 (580-1,360)
t½ (days) | 27.6 (5.9) | 27.8 (21.6-33.4) | 45.4 (18.5) | 37.3 (20.6-96.6)
AUC0-t (day × mg/dL) [Calculated by log-linear trapezoidal rule.] | 32,820 (6,260) | 29,860 (28,580-40,010) | 36,390 (5,950) | 36,670 (19,680-44,340)
AUC0-∞ (day × mg/dL) | 79,315 (20,170) | 78,748 (59,435-99,762) | 104,627 (33,581) | 98,521 (64,803-178,600)
Clearance (mL/day/kg) | 1.3 (0.1) | 1.3 (1.1-1.4) | 1.3 (0.3) | 1.3 (0.9-2.1)
Mean residence time (days) | 38.6 (8.1) | 39.5 (30.1-46.2) | 65.2 (24.7) | 59.0 (33.2-129.6)
Volume of distribution at steady state (mL/kg) | 50 (13) | 44 (40-65) | 84 (35) | 87 (40-207)
Cmax, maximum serum concentration; Cmin, trough (minimum level) serum concentration; t½, elimination half-life; AUC0-t, area under the curve from 0 hour to last sampling time; AUC0-∞, area under the curve from 0 hour to infinite time.

Although no systematic study was conducted to evaluate the effect of gender and age on the pharmacokinetics of PRIVIGEN, based on the small sample size (11 males and 14 females), it appears that clearance of PRIVIGEN is comparable in males (1.27 ± 0.35 mL/day/kg) and females (1.34 ± 0.22 mL/day/kg). In six subjects between 13 and 15 years of age, the clearance of PRIVIGEN (1.35 ± 0.44 mL/day/kg) is comparable to that observed in 19 adult subjects 19 years of age or older (1.29 ± 0.22 mL/day/kg). The IgG subclass levels observed in the pharmacokinetic study were consistent with a physiologic distribution pattern.

Treatment of Chronic Immune Thrombocytopenic Purpura

Pharmacokinetic studies with PRIVIGEN were not performed in subjects with chronic ITP.

Treatment of Chronic Inflammatory Demyelinating Polyneuropathy

Trough concentrations:

In both the PRIMA and PATH studies, on Day 1, subjects received an induction dose (2 g/kg) given over 2 to 5 days, followed by maintenance doses of 1 g/kg every 3 weeks.

In the PRIMA study, from Day 1 (reference) to Day 2, the mean serum IgG trough concentration increased from 12.6 ± 3.8 g/L to 24.4 ± 7.0 g/L. At Week 7, before the second maintenance treatment of (1 g/kg) given over 1 or 2 days every 3 weeks, the mean IgG trough concentration was 17.5 ± 3.1 g/L and remained stable from Week 7 to Week 19.

In the PATH study, from Day 1 (reference) to Day 5, the mean serum IgG trough concentration increased from 12.7 ± 3.2 g/L to 33.2 ± 6.9 g/L. At Week 7, before the second maintenance treatment of (1 g/kg) given over 1 or 2 days every 3 weeks, the mean IgG trough concentration was 17.7 ± 4.0 g/L and remained stable from Week 7 to Week 13.

Post-infusion concentrations:

In the PRIMA study, from Day 1 to Day 2, the post-infusion serum IgG concentration increased from 28.6 ± 8.5 g/L to 40.0 ± 11.5 g/L. At Week 7 (after the second maintenance treatment), the post-infusion IgG concentration was 32.3 ± 8.0 g/L and remained stable from Week 7 to Week 19.

14 CLINICAL STUDIES

14.1 Treatment of Primary Humoral Immunodeficiency

A prospective, open-label, single-arm, multicenter study assessed the efficacy, safety, and pharmacokinetics of PRIVIGEN in adult and pediatric subjects with PI, who were treated for 12 months at a 3-week or 4-week dosing interval. Subjects ranged in age from 3 to 69; 46 (57.5%) were male and 34 (42.5%) were female; 77.5% were Caucasian, 15% were Hispanic, and 7.5% were African-American. All subjects had been on regular IGIV replacement therapy for at least 6 months prior to participating in the study.

The efficacy analysis included 80 subjects, 16 (20%) on the 3-week dosing interval and 64 (80%) on the 4-week dosing interval. Doses ranged from 200 mg/kg to 888 mg/kg per infusion. The median dose for the 3-week interval was 428.3 mg/kg per infusion; the median dose for the 4-week interval was 440.6 mg/kg per infusion. Subjects received a total of 1038 infusions of PRIVIGEN, 272 for the 3-week dosing regimen and 766 for the 4-week dosing regimen. The maximum infusion rate allowed during this study was 8 mg/kg/min with 715 (69%) of the infusions administered at a rate of 7 mg/kg/min or greater.

The primary analysis for efficacy was based on the annual rate of acute serious bacterial infections (aSBIs), defined as pneumonia, bacteremia/septicemia, osteomyelitis/septic arthritis, bacterial meningitis, and visceral abscess, per subject per year. Secondary analyses were based on the annual rate of other infections, antibiotic use, days out of work/school/day care or unable to perform normal activities due to illness, and days of hospitalization.

During the 12-month study period, the aSBI rate was 0.08 (with an upper 1-sided 99% confidence interval of 0.203), which met the predefined success rate of less than one aSBI per subject per year. Six subjects experienced an aSBI, including three cases of pneumonia and one case each of septic arthritis, osteomyelitis, and visceral abscess. All six subjects completed the study.

The rate of other infections was 3.55 infections per subject per year. The infections that occurred most frequently were sinusitis (31.3%), nasopharyngitis (22.5%), upper respiratory tract infection (18.8%), bronchitis (13.8%), and rhinitis (13.8%). Among the 255 infections, 16 (6.3%) occurring in 10 subjects were considered severe.

Table 8 summarizes the efficacy results for all 80 subjects.

Table 8. PI Study – Summary of Efficacy Results in Subjects
Number of Subjects | 80
Results from Case Report Forms
Total Number of Subject Days | 26,198
Infections
Annual rate of confirmed aSBIs [Defined as pneumonia, bacterial meningitis, bacteremia/septicemia, osteomyelitis/septic arthritis, and visceral abscess.] | 0.08 aSBIs/subject year [Upper 1-sided 99% confidence interval: 0.203.]
Annual rate of other infections | 3.55 infections/subject year
Antibiotic use
Number of subjects (%) | 64 (80%)
Annual rate | 87.4 days/subject year
Results from Subject Diaries
Total Number of Diary Days | 24,059
Out of work/school/day care or unable to perform normal activities due to illness
Number of days (%) | 570 (2.37%)
Annual rate | 8.65 days/subject year
Hospitalization
Number of days (%) | 166 (0.69%)
Annual rate | 2.52 days/subject year

14.2 Treatment of Chronic Immune Thrombocytopenic Purpura

A prospective, open-label, single-arm, multicenter study assessed the efficacy, safety, and tolerability of PRIVIGEN in 57 subjects with chronic ITP and a platelet count of 20 × 10^9/L or less. Subjects ranged in age from 15 to 69; 23 (40.4%) were male and 34 (59.6%) were female; all were Caucasian.

Subjects received a 2 g/kg dosage of PRIVIGEN administered as 1 g/kg (10 mL/kg) intravenous infusion daily for 2 consecutive days, and were observed for 29 days. Fifty-three (93%) subjects received PRIVIGEN at the maximum infusion rate allowed (4 mg/kg/min [0.04 mL/kg/min]).

The primary analysis was based on the response rate defined as the percentage of subjects with an increase in platelet counts to at least 50 × 10^9/L within 7 days after the first infusion (responders). Secondary analyses were based on the increase in platelet counts and the time to reach a platelet count of at least 50 × 10^9/L at any point within the study period, the duration of that response, and the regression (decrease in the severity) of hemorrhage in subjects who had bleeding at baseline. Platelet counts were measured on Days 1, 2, 4, 6, 8, 15, 22, and 29. Additional measurements on Days 57 and 85 occurred in subjects with a platelet count of at least 50 × 10^9/L at the previous visit.

Of the 57 subjects in the efficacy analysis, 46 (80.7%) responded to PRIVIGEN with a rise in platelet counts to at least 50 × 10^9/L within 7 days after the first infusion. The lower bound of the 95% confidence interval for the response rate (69.2%) is above the predefined response rate of 50%.

The highest median increase in platelet counts was seen 7 days after the first infusion (123 × 10^9/L). The median maximum platelet count achieved was 154 × 10^9/L. The median time to reach a platelet response of more than 50 × 10^9/L was 2.5 days after the first infusion. Twenty-five (43%) of the 57 subjects reached this response by Day 2 prior to the second infusion and 43 (75%) subjects reached this response by Day 6.

The duration of platelet response was analyzed for the 48 subjects who achieved a response any time after the first infusion. The median duration of platelet response in these subjects was 15.4 days (range: 1 to >82 days). Thirty-six (75%) of the 48 subjects maintained the response for at least 8.8 days and 12 (25%) of them for at least 21.9 days. Five (9%) subjects maintained a response up to Day 29 and two (4%) up to Day 85.

A decrease in the severity of hemorrhage from baseline was observed in the following bleeding locations: skin (31 of 36 subjects), oral cavity (11 of 11 subjects), and genitourinary tract (7 of 9 subjects). This decrease was not sustained in all subjects up to the end of the 29-day study period.

14.3 Postmarketing Commitment Study in Chronic Immune Thrombocytopenic Purpura

A prospective, open-label, single-arm, multicenter study assessed efficacy and safety parameters in 57 IGIV-treated subjects with chronic ITP with a platelet count of <30 × 10^9/L at screening. Fifty-three subjects had a history of chronic ITP with a duration of greater than 6 months and 4 subjects, all of whom had received prior treatment for ITP with subsequent elevation followed by falls in platelet counts, had a duration of ITP less than 6 months. The study examined the incidence of subjects who met laboratory and clinical criteria for hemolysis and was intended to identify antibodies most frequently bound to erythrocytes in subjects who experienced clinically significant intravascular hemolysis. Subjects ranged in age from 18 to 65; 20 (35.1%) were male and 37 (64.9%) were female; all were Caucasian.

Twenty-one (21) subjects (37%) received 1 infusion of 1 g/kg on Day 1 and 36 subjects (63%) received 2 infusions of 1 g/kg (Day 1 and Day 3). The second infusion was administered based on the subject's platelet response to the Day 1 dose (<50 × 10^9/L) and investigator's discretion.

The efficacy endpoint platelet response (increase in platelet count at least once to at least 50 × 10^9/L within 6 days after the first infusion) was achieved in 42 subjects (74%; 95% confidence interval [CI]: 61% to 83%).

Fifteen subjects with a suspicion of hemolysis based on laboratory data were referred for independent expert adjudication during the study. The adjudication committee selected from 3 options for their determination: no hemolysis, hemolysis, or clinically significant intravascular hemolysis. The set of antibodies most frequently bound to erythrocytes in subjects with clinically significant intravascular hemolysis could not be analyzed, because no subject experienced clinically significant intravascular hemolysis. No irregular antibodies were detected in any subject; therefore, no association between such antibodies and hemolytic laboratory changes could be established. Hemolytic laboratory changes were most often found in non-O blood group (especially the A blood group) subjects and those receiving 2 infusions. These laboratory parameters improved or normalized by the end of the study in the majority of subjects. Seven subjects (12% of the study population) with a normal hemoglobin at baseline had an abnormal hemoglobin at Day 29 (end of study) with a hemoglobin range from 11.2 to 13.6 g/dL.

Post-hoc analyses were performed using a set of defined criteria for hemolysis. The hemolysis group (18 subjects, 32%) met the criterion for greater than 1 g/dL drop in hemoglobin within a 21-day interval since the last IGIV administration not explained by blood loss or repeated phlebotomy, were treatment-emergent DAT positive, and met at least one other minor criterion (eg, fall in serum haptoglobin level to below the lower limit of normal, rise in lactate dehydrogenase level above the upper limit of normal, rise in indirect or total bilirubin to above the upper limit of normal, or rise in plasma-free hemoglobin above the upper limit of normal). Fourteen of 15 previously adjudicated presumptive hemolysis cases during the study were included in this post-hoc hemolysis group.

14.4 Treatment of Chronic Inflammatory Demyelinating Polyneuropathy

In a prospective, open-label, single-arm, multicenter clinical study (PRIVIGEN Impact on Mobility and Autonomy [PRIMA]), 28 subjects with CIDP (13 IGIV-pretreated and 15 IGIV-untreated) received a PRIVIGEN loading dose of 2 g/kg followed by PRIVIGEN maintenance doses of 1 g/kg for up to 21 weeks with a 3 week follow up.

Efficacy in the PRIMA study was based on the responder rate of PRIVIGEN in comparison to an historical control in the adjusted 10-point Inflammatory Neuropathy Cause and Treatment (INCAT) score.^19 The responder rate was defined as the proportion of subjects who demonstrated clinically meaningful improvement (at least 1 point decrease on adjusted Inflammatory Neuropathy Cause and Treatment [INCAT] score) between baseline and Week 25, with a pre-specified threshold of 35% in the lower limit of the 2-sided 95% Wilson-Score confidence interval (CI). The overall percentage of responders in PRIMA was 61% (95% CI: 42.4% to 76.4%). Response rates were 47% in IGIV-untreated and 77% in IGIV-pretreated subject subgroups. In a post-hoc analysis, the overall percentage of subjects in PRIMA who responded by week 10 and maintained the response through week 25 and lacked confounding changes in glucocorticoid/immunosuppressant dosage was 53.6% (95% CI: 35.8% to 70.5%).

In a second study (PATH) with the same PRIVIGEN dosing regimen, all 207 subjects were IGIV-pretreated and had relapsed following withdrawal of IGIV prior to being administered PRIVIGEN [see Dosage and Administration (2.3)]. The response rate was 73% (see Figure 1). Among the subset of 151 subjects in the PATH study who had deteriorated by one or more points in adjusted INCAT score following withdrawal of IGIV, 137 subjects (90.7%) responded during the PRIVIGEN "restabilization" period with an increase of one or more adjusted INCAT score points.

The overall median time to first adjusted INCAT response in PRIMA was 7.5 weeks (18 weeks in IGIV-untreated and 3 weeks in IGIV-pretreated). The median time to first adjusted INCAT response in PATH (all IGIV-pretreated) was 3.7 weeks (95% CI: 3.4 to 5.9 weeks). Mean INCAT score in PRIMA showed a clinically meaningful improvement by 1.4 points (1.1 points for IGIV-untreated, and 1.8 points for IGIV-pretreated [1.2 points in PATH]).

Figure 1. Percentage of Responders (Adjusted INCAT Score)

Medical Research Council (MRC) sum score in PRIMA improved by a mean of 6.9 points (7.7 points for IGIV-untreated and 6.1 points for IGIV-pretreated). MRC sum score in PATH improved by a mean of 3.6 points.

Grip strength of the dominant hand improved in PRIMA by a mean of 14.1 kPa (17.0 kPa for IGIV-untreated and 10.8 kPa for IGIV-pretreated subgroups). Grip strength of the dominant hand improved in PATH by a mean of 12.2 kPa. Similar results were observed for the non-dominant hand in both studies.

15 REFERENCES

1. Dalakas MC. High-dose intravenous immunoglobulin and serum viscosity: risk of precipitating thromboembolic events. Neurology 1994;44:223-226.
2. Woodruff RK, Grigg AP, Firkin FC, Smith IL. Fatal thrombotic events during treatment of autoimmune thrombocytopenia with intravenous immunoglobulin in elderly patients. Lancet 1986;2:217-218.
3. Wolberg AS, Kon RH, Monroe DM, Hoffman M. Coagulation factor XI is a contaminant in intravenous immunoglobulin preparations. Am J Hematol 2000;65:30-34.
4. Cayco AV, Perazella MA, Hayslett JP. Renal insufficiency after intravenous immune globulin therapy: a report of two cases and an analysis of the literature. J Am Soc Nephrol 1997;8:1788-1793.
5. Steinberger BA, Ford SM, Coleman TA. Intravenous immunoglobulin therapy results in post-infusional hyperproteinemia, increased serum viscosity, and pseudohyponatremia. Am J Hematol 2003;73:97-100.
6. Gabor EP. Meningitis and skin reaction after intravenous immune globulin therapy. Ann Intern Med 1997;127:1130.
7. Copelan EA, Strohm PL, Kennedy MS, Tutschka PJ. Hemolysis following intravenous immune globulin therapy. Transfusion 1986;26:410-412.
8. Thomas MJ, Misbah SA, Chapel HM, Jones M, Elrington G, Newsom-Davis J. Hemolysis after high-dose intravenous Ig. Blood 1993;15:3789.
9. Wilson JR, Bhoopalam N, Fisher M. Hemolytic anemia associated with intravenous immunoglobulin. Muscle Nerve 1997;20:1142-1145.
10. Kessary-Shoham H, Levy Y, Shoenfeld Y, Lorber M, Gershon H. In vivo administration of intravenous immunoglobulin (IVIg) can lead to enhanced erythrocyte sequestration. J Autoimmun 1999;13:129-135.
11. Kahwaji J, Barker E, Pepkowitz S, et al. Acute Hemolysis After High-Dose Intravenous Immunoglobulin Therapy in Highly HLA Sensitized Patients. Clin J Am Soc Nephrol 2009;4:1993-1997.
12. Daw Z, Padmore R, Neurath D, et al. Hemolytic transfusion reactions after administration of intravenous immune (gamma) globulin: A case series analysis. Transfusion 2008;48:1598-1601.
13. Rizk A, Gorson KC, Kenney L, Weinstein R. Transfusion-related acute lung injury after the infusion of IVIG. Transfusion 2001;41:264-268.
14. Pierce LR, Jain N. Risks associated with the use of intravenous immunoglobulin. Trans Med Rev 2003;17:241-251.
15. Siber GA, Werner BG, Halsey NA, et al. Interference of immune globulin with measles and rubella immunization. J Pediatr 1993;122:204-211.
16. Hammarström L, Smith CIE. Placental transfer of intravenous immunoglobulin. Lancet 1986;1:681.
17. Sidiropoulos D, Herrmann U, Morell A, von Muralt G, Barandun S. Transplacental passage of intravenous immunoglobulin in the last trimester of pregnancy. J Pediatr 1986;109:505-508.
18. Gregori L, Maring J-A, MacAuley C, Stühler A, Löwer J, Blümel J. Partitioning of TSE infectivity during ethanol fractionation of human plasma. Biologicals 2004;32:1-10.
19. Hughes RAC, Donofrio P, Bril V, et al. Intravenous immune globulin (10% caprylate/chromatography purified) for the treatment of chronic inflammatory demyelinating polyradiculoneuropathy (ICE study): a randomised placebo-controlled trial. Lancet Neurol 2008;7:136-44.

16 HOW SUPPLIED/STORAGE AND HANDLING

PRIVIGEN is supplied in a single-use, tamper-evident vial containing the labeled amount of functionally active IgG. The PRIVIGEN packaging components are not made with natural rubber latex.

Each product presentation includes a package insert and the following components:

Table 9. How Supplied
Presentation | Carton NDC Number | Components
50 mL | 44206-436-05 | Vial containing 5 grams of protein (NDC 44206-436-90)
100 mL | 44206-437-10 | Vial containing 10 grams of protein (NDC 44206-437-91)
200 mL | 44206-438-20 | Vial containing 20 grams of protein (NDC 44206-438-92)
400 mL | 44206-439-40 | Vial containing 40 grams of protein (NDC 44206-439-93)

Storage and Handling

- Keep PRIVIGEN in its original carton to protect it from light.
- Each vial has an integral suspension band and a label with two peel-off strips showing the product name, lot number, and expiration date.
- When stored at room temperature (up to 25ºC [77ºF]), PRIVIGEN is stable for up to 36 months, as indicated by the expiration date printed on the outer carton and vial label.
- Do not freeze.

17 PATIENT COUNSELING INFORMATION

Inform patients of the early signs of hypersensitivity reactions to PRIVIGEN (including hives, generalized urticaria, tightness of the chest, wheezing, hypotension, and anaphylaxis), and advise them to notify their physician if they experience any of these symptoms [see Warnings and Precautions (5.1)].

Inform patients to immediately report the following signs and symptoms to their physician:

- Decreased urine output, sudden weight gain, fluid retention/edema, and/or shortness of breath, which may suggest kidney problems [see Warnings and Precautions (5.2)].
- Instruct patients to immediately report symptoms of thrombosis. These symptoms may include: pain and/or swelling of an arm or leg with warmth over the affected area, discoloration of an arm or leg, unexplained shortness of breath, chest pain or discomfort that worsens on deep breathing, unexplained rapid pulse, numbness or weakness on one side of the body [see Warnings and Precautions (5.3)].
- Severe headache, neck stiffness, drowsiness, fever, sensitivity to light, painful eye movements, nausea, and vomiting, which may suggest aseptic meningitis syndrome [see Warnings and Precautions (5.5)].
- Fatigue, increased heart rate, yellowing of skin or eyes, and dark-colored urine, which may suggest hemolysis [see Warnings and Precautions (5.6)].
- Severe breathing problems, lightheadedness, drops in blood pressure, and fever, which may suggest TRALI (a condition typically occurring within 1 to 6 hours following transfusion) [see Warnings and Precautions (5.8)].

Inform patients that PRIVIGEN is made from human blood and may contain infectious agents that can cause disease (eg, viruses, the variant Creutzfeldt-Jakob disease [vCJD] agent and, theoretically the CJD agent). Explain that the risk that PRIVIGEN may transmit an infectious agent has been reduced by screening the plasma donors, by testing donated plasma for certain virus infections, and by inactivating or removing certain viruses during manufacturing, and counsel patients to report any symptoms that concern them [see Warnings and Precautions (5.10)].

Inform patients that administration of IgG may interfere with the response to live virus vaccines (eg, measles, mumps, rubella, and varicella), and instruct them to notify their immunizing physician of recent therapy with PRIVIGEN [see Warnings and Precautions (5.11)].

Manufactured by:
CSL Behring AG
Bern, Switzerland
US License No. 1766

Distributed by:
CSL Behring LLC
Kankakee, IL 60901 USA

PRINCIPAL DISPLAY PANEL - 50 mL Vial Carton

NDC 44206-436-05
5 g

Immune Globulin
Intravenous (Human),
10% Liquid
50 mL

privigen®

10% Liquid Preparation
Single-dose vial

For Intravenous Administration
only

Rx only

CSL Behring

PRINCIPAL DISPLAY PANEL - 100 mL Vial Carton

NDC 44206-437-10
10 g

Immune Globulin
Intravenous (Human),
10% Liquid
100 mL

privigen®

10% Liquid Preparation
Single-dose vial

For Intravenous Administration
only

Rx only

CSL Behring

PRINCIPAL DISPLAY PANEL - 200 mL Vial Carton

NDC 44206-438-20
20 g

Immune Globulin
Intravenous (Human),
10% Liquid
200 mL

privigen®

10% Liquid Preparation
Single-dose vial

For Intravenous Administration
only

Rx only

CSL Behring

PRINCIPAL DISPLAY PANEL - 400 mL Vial Carton

NDC 44206-439-40
40 g

Immune Globulin
Intravenous (Human),
10% Liquid
400 mL

privigen®

10% Liquid Preparation
Single-dose vial

For Intravenous Administration
only

Rx only

CSL Behring